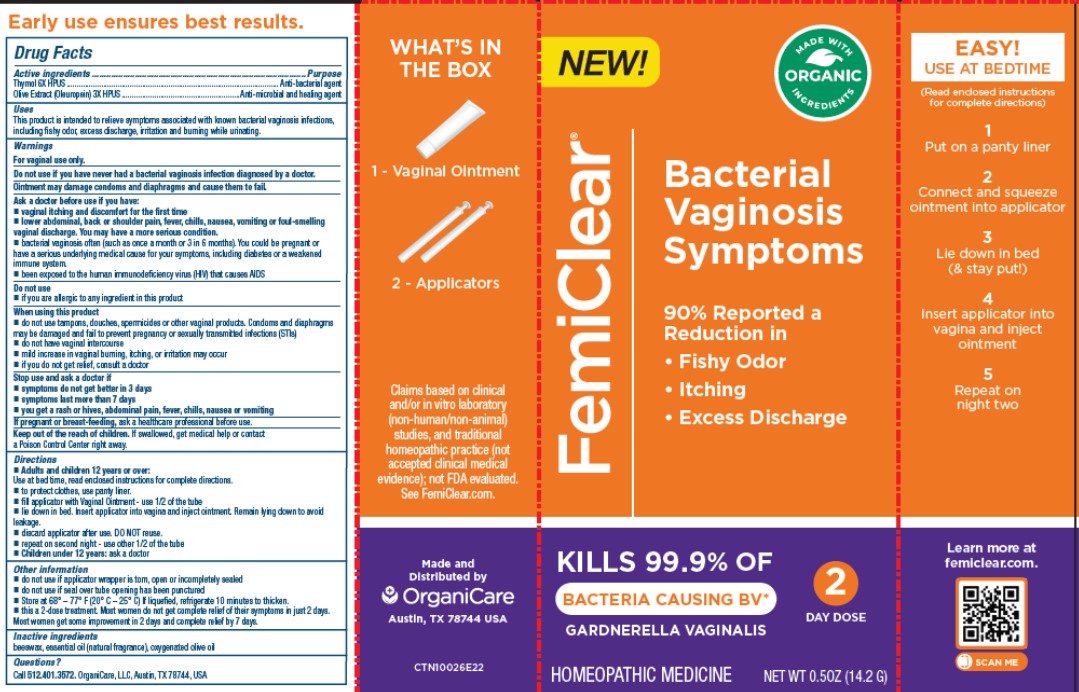 DRUG LABEL: FemiClear Bacterial Vaginosis Symptoms
NDC: 71042-025 | Form: OINTMENT
Manufacturer: Organicare Nature's Science, LLC
Category: homeopathic | Type: HUMAN OTC DRUG LABEL
Date: 20251020

ACTIVE INGREDIENTS: THYMOL 6 [hp_X]/100 g; OLEA EUROPAEA FRUIT VOLATILE OIL 3 [hp_X]/100 g
INACTIVE INGREDIENTS: YELLOW WAX; OLIVE OIL

FemiClear Bactgerial Vaginosis Symptoms

Active Ingredients

Thymol 6X HPUS

Olive Extract (Oleuropein) 3X HPUS

Purpose

Anti-bacterial agent

Anti-microbial and Healing agent

Uses

This product is intended to relieve symptoms associated with known bacterial vaginosis infecions, including fishy odor, excess discharge, irritation and burning while urinating.

Warnings

For vaginal use only.

Do not use if you have never had a bacterial vaginosis infection diagnosed by a doctor.

Ointment may damage condoms and diaphragms and cause them to fail.

Ask a doctor before use if you have:

- vaginal itching and discomfort for the first time
- lower abdominal, back or shoulder pain, fever, chills, nausea, vomiting or foul-smelling vaginal discharge. You may have a more serious condition.
- bacterial vaginosis often (such as once a month or 3 in 6 months). You could be pregnant or have a serious underlying medical cause for your symptoms, including diabetes or a weakened immune system.
- been exposed to the human immunodeficiency virus (HIV) that causes AIDS.

Do not use

if you are allergic to any ingredient in this product

When using this product

- do not use tampons, douches, spermicides or other vaginal products. Condoms and diaphragms may be damaged and fail to prevent pregnancy or sexually transmitted infections (STIs)
- do not have vaginal intercourse
- mild increase in vaginal burning, itching, or irritation may occur
- if you do not get relief, consult a doctor

Stop use and ask a doctor if

- symptoms do not get better in 3 days
- symptoms last more than 7 days
- you get a rash or hives, abdominal pain, fever, chills, nausea or vomiting

If pregnant or breast-feeding

ask a healthcare professional before use.

Keep out of the reach of children

If swallowed, get medical help or contact Poison Control Center right away

Directions

Adults and children 12 years of age and older:

- Use at bed time, read enclosed instructions for complete directions.
- to protect clothes, use a panty liner.
- fill applicator with Vaginal Ointment - use 1/2 of the tube
- lie down in bed. Insert applicator into vagina and inject ointment. Remain lying down to avoid leakage.
- discard applicator after use. DO NOT reuse.
- repeat on second night - use other 1/2 of the tube

Children under 12 years: ask a doctor

Other Information

- do not use if applicator wrapper is torn, open or incompletely sealed
- do not use if seal over tube opening has been punctured
- Store at 68°-77°F (20°C - 25°C) If liquified, refrigerate 10 minutes to thicken.
- this is a 2-dose treatment. Most women do not get complete relief of their symptoms in just 2 days.

Most women get some improvement in 2 days and complete relief by 7 days.

Inactve ingredients

beeswax, essential oil (natural fragrance), oxygenated olive oil

Questions?

Call 512.401.3572 or visit femiclear.com

Made and Distributed by OrganiCare, LLC

Austin, TX 78744, USA

Claims based on clinical and/or in vitro laboratory

(non-human/non-animal) studies, and traditional homeopathic practice (not accepted clinical medical evidence; not FDA evaluated).

See FemiClear.com

Made and Distributed by

Organicare

Austin, TX 78744, USA

PACKAGE LABEL

FemiClear®

Bacterial Vaginosis Symptoms

90% Reported a Reduction in

- Fishy Odor
- Itching
- Excess Discharge

MADE WITH ORGANIC INGREDIENTS

KILLS 99.9% OF BACTERIA CAUSING BV

GARDNERELLA VAGINALIS

HOMEOPATHIC MEDICINE